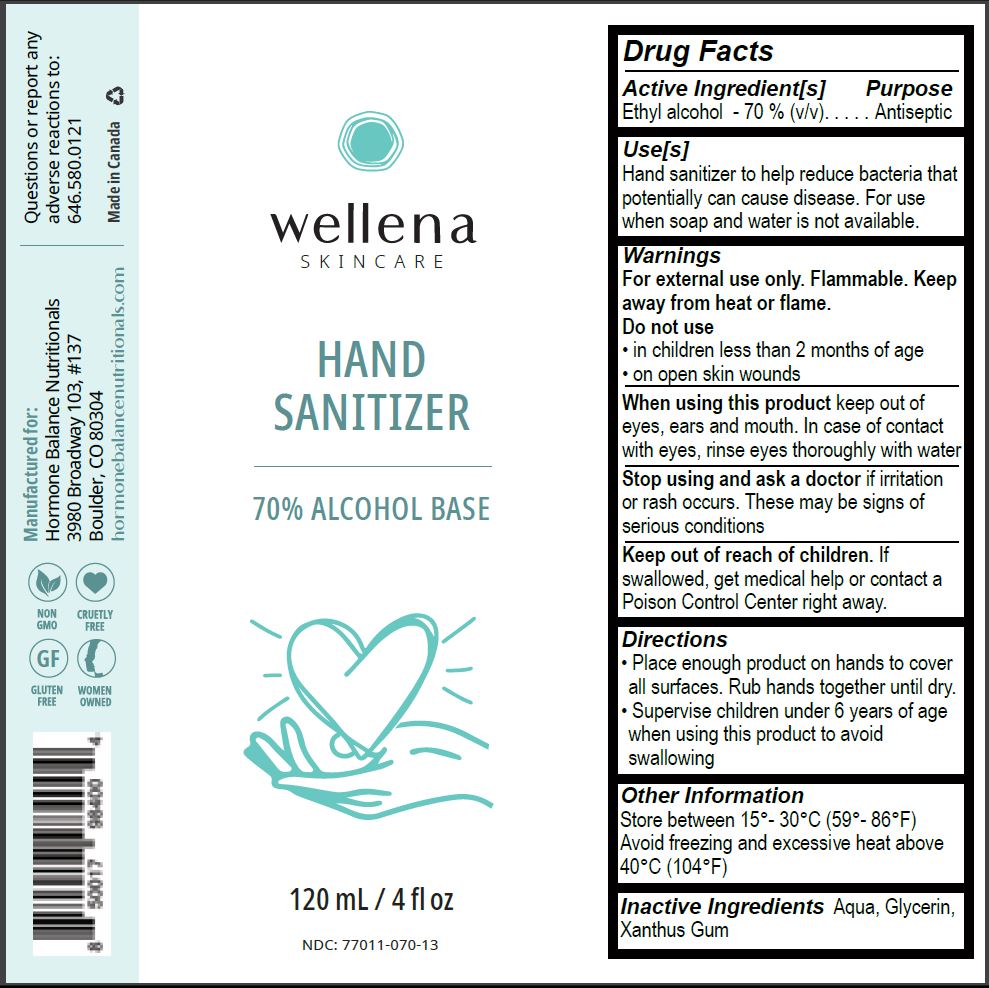 DRUG LABEL: wellena skincare hand sanitizer
NDC: 77011-070 | Form: LIQUID
Manufacturer: Hormone Balance Nutritionals
Category: otc | Type: HUMAN OTC DRUG LABEL
Date: 20200508

ACTIVE INGREDIENTS: ALCOHOL 0.7 mL/1 mL
INACTIVE INGREDIENTS: WATER; XANTHAN GUM; GLYCERIN

wellena
SKINCARE
Hand Sanitizer

Active Ingredient[s]

Ethyl alcohol - 70 % (v/v)

Purpose

Antiseptic

Use[s]

Hand sanitizer to help reduce bacteria that potentially can cause disease. For use when soap and water is not available.

Warnings

For external use only. Flammable. Keep away from heat or flame.

Do not use

- in children less than 2 months of age
- on open skin wounds

When using this product keep out of eyes, ears and mouth. In case of contact with eyes, rinse eyes thoroughly with water

STOP USE

Stop using and ask a doctor if irritation or rash occurs. These may be signs of serious conditions.

Keep out of reach of children. If swallowed, get medical help or contact a Poison Control Center right away.

Directions

- Place enough product on hands to cover all surfaces. Rub hands together until dry.
- Supervise children under 6 years of age when using this product to avoid swallowing

Other Information

Store between 15°-30°C (59°-86°F)

Avoid freezing and excessive heat above 40°C (104°F)

Inactive Ingredients

Aqua, Glycerin, Xanthan Gum

wellena SKINCARE Hand Sanitizer - 120 mL

wellena

SKINCARE

HAND SANITIZER

70% ALCOHOL BASE

120 mL / 4 fl oz

NDC: 77011-070-13

Questions or report any adverse reactions to:

646.580.0121

Made in Canada

Manufactured for:

Hormone Balance Nutritionals

3980 Broadway 103, #137

Boulder, CO 80304

hormonebalancenutrionals.com

NONGMO

CRUELTY FREE

GLUTEN FREE

WOMEN OWNED